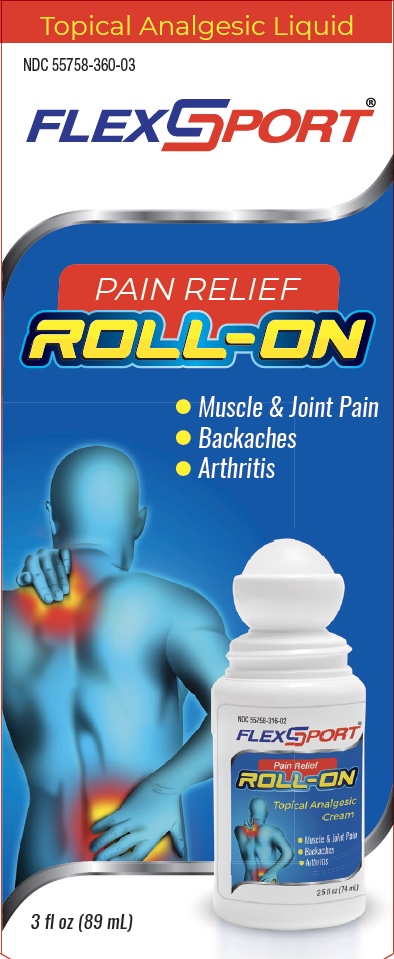 DRUG LABEL: FlexSport Roll On
NDC: 55758-360 | Form: LIQUID
Manufacturer: Pharmadel LLC
Category: otc | Type: HUMAN OTC DRUG LABEL
Date: 20251204

ACTIVE INGREDIENTS: METHYL SALICYLATE 15 g/100 g
INACTIVE INGREDIENTS: CAPSAICIN; PROPYLENE GLYCOL; WATER; ISOPROPYL ALCOHOL; MENTHOL; POLYSORBATE 20; ALPHA-TOCOPHEROL ACETATE; CAMPHOR (SYNTHETIC); POLYACRYLIC ACID (250000 MW); DMDM HYDANTOIN; ARNICA MONTANA FLOWER; TROLAMINE; EUCALYPTUS OIL

FlexSport Roll On - MS 15% (WP)(DA)

Active ingredient and Purpose

Active ingredient | Purpose
Menthol 16% .................... | Topical analgesic

Uses

For the temporary relief of minor aches and pains of muscles and joints associated with:

- arthritis
- simple backache
- muscle strains
- sprains
- bruises

Warnings

For external use only. Avoid contact with the eyes.

Flammable: keep away from fire or flame.

When using this product

- do not bandage tightly or use with a heating pad
- do not apply to wounds or damaged, broken or irritated skin

Stop use and ask a doctor if

- condition worsens
- redness is present
- irritation develops
- symptoms persist for more than 7 days or clear up and occur again within a few days

If pregnant or breast-feeding,

ask a health professional before use.

Keep out of reach of children.

If swallowed,get medical help or contact a Poison Control Center right away.

Directions

- use only as directed
- adults and children over 12 years: apply to affected area not more than 3 to 4 times daily
- children under 12 years of age: ask a doctor

Other information

- store at temperatures not exceeding 15°–30°C (59°– 86°F)
- avoid excessive heat and humidity

Inactive ingredients

acrylates/C10-30 alkyl acrylate crosspolymer, alcohol, capsaicin, glycerin, isopropyl myristate, propylene glycol, trolamine, water

Questions or Comments?

1-866-359-3478 (M-F) 9 AM – 5 PM EST or www.pharmadel.com

Principal Display Panel

Topical Analgesic Liquid

FlexSport

Pain Relief

ROLL-ON

- Muscle & Joint Pain
- Backaches
- Arthritis

3 fl oz (89 mL)